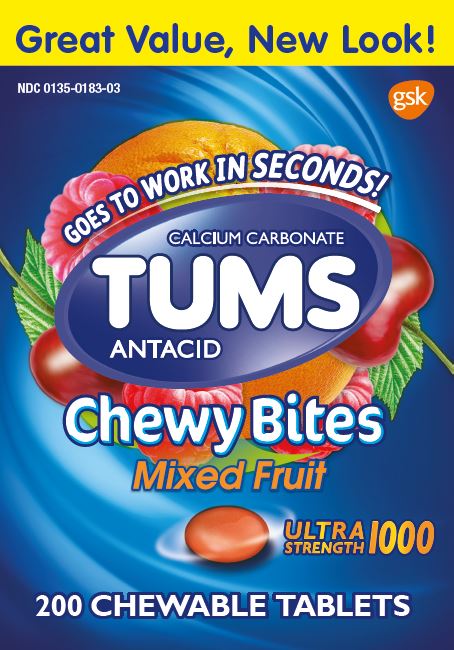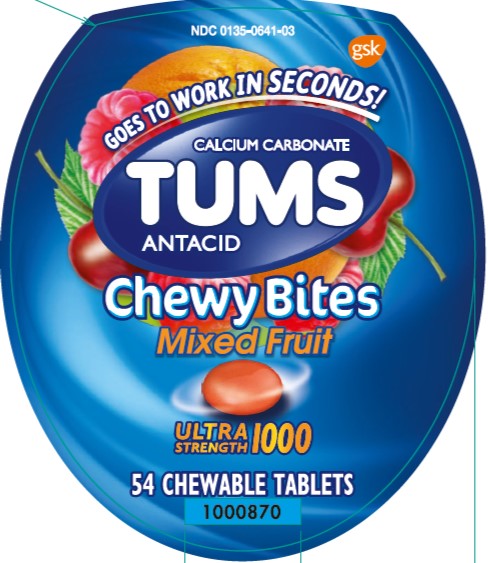 DRUG LABEL: Tums Chewy Bites

NDC: 0135-0641 | Form: TABLET, CHEWABLE
Manufacturer: Haleon US Holdings LLC
Category: otc | Type: HUMAN OTC DRUG LABEL
Date: 20240302

ACTIVE INGREDIENTS: CALCIUM CARBONATE 1000 mg/1 1
INACTIVE INGREDIENTS: ALCOHOL; AMMONIA; YELLOW WAX; CARMINIC ACID; CARNAUBA WAX; CITRIC ACID MONOHYDRATE; COCONUT OIL; STARCH, CORN; CORN SYRUP; ICODEXTRIN; ETHYL ACETATE; FD&C BLUE NO. 1; ALUMINUM OXIDE; FD&C BLUE NO. 2; FD&C RED NO. 40; FD&C YELLOW NO. 5; FD&C YELLOW NO. 6; ACACIA; ISOPROPYL ALCOHOL; MALTODEXTRIN; MEDIUM-CHAIN TRIGLYCERIDES; METHYLPARABEN; MODIFIED CORN STARCH (1-OCTENYL SUCCINIC ANHYDRIDE); BUTYL ALCOHOL; PHOSPHORIC ACID; POVIDONE, UNSPECIFIED; PROPYLENE GLYCOL; PROPYLPARABEN; WATER; SHELLAC; SODIUM BENZOATE; SORBIC ACID; SORBITOL; LECITHIN, SOYBEAN; SUCROSE; TITANIUM DIOXIDE; TRIACETIN; CORN OIL

Drug Facts

Active ingredient

Calcium carbonate 1000mg

Purpose

Antacid

Uses

relieves

- heartburn
- acid indigestion
- sour stomach
- upset stomach associated with these symptoms

Warnings

Ask a doctor or pharmacist before use if you are

presently taking a prescription drug. Antacids may interact with certain prescription drugs.

When using this product

- do not take more than 4 tablets in 24 hours
- if pregnant do not take more than 4 tablets in 24 hours
- do not use the maximum dosage for more than 2 weeks except, under the advice and supervision of a doctor

Directions

- adults and children 12 years of age and over:chew 2-3 tablets as symptoms occur, or as directed by a doctor. Chew or crush tablets completely before swallowing.
- do not take for symptoms that persist for more than 2 weeks unless advised by a doctor

Other information (54 ct. Bottle)

- each chewable tablet contains:elemental calcium 400 mg
- do not store above 25°C (77°F)

Other information (200 ct. Bottle)

- each chewable tablet contains:elemental calcium 400 mg
- do not store above 25°C (77°F)
- contains FD&C Yellow No. 5 (tartrazine) as a color additive

Inactive ingredients

alcohol, ammonium hydroxide, beeswax, carmine, carnauba wax, citric acid, coconut oil, corn starch, corn syrup, dextrin, ethyl acetate, FD&C blue no. 1 aluminum lake, FD&C blue no.2 aluminum lake, FD&C red no.40, FD&C red no.40 aluminum lake, FD&C yellow no.5 aluminum lake (tartrazine), FD&C yellow no.6, FD&C yellow no.6 aluminum lake, flavors, gum arabic, isopropyl alcohol, maltodextrin, medium-chain triglycerides, methylparaben, modified starch, n-butyl alcohol, phosphoric acid, polyvinylpyrrolidone, propylene glycol, propylparaben, purified water, shellac, sodium benzoate, sorbic acid, sorbitol, soy lecithin, sucrose, titanium dioxide, triacetin, vegetable oil

Questions or comments?

1-800-897-7535

Principal Display Panel (54 ct. Bottle)

NDC 0135-0641-03

TUMS

CALCIUM CARBONATE

ANTACID

Chewy Bites

Mixed Fruit

ULTRA STRENGTH 1000

GOES TO WORK IN SECONDS!

54 CHEWABLE TABLETS

Safety sealed – Do not use if printed inner safety seal under cap is broken or missing.

Distributed by:

GSKConsumer Healthcare

Warren, NJ 07059

Trademarks are owned by or licensed to the GSK group of companies.

©2020 GSK group of companies or its licensor

Front Label: 1000870

Back Label: 1000871

Principal Display Panel (200 ct. Bottle)

Great Value, New Look!

NDC 0135-0183-03

GOES TO WORK IN SECONDS!

CALCIUM CARBONATE

TUMS

ANTACID

Chewy Bites

Mixed Fruit

Ultra Strength 1000

200 CHEWABLE TABLETS

Safety sealed – Do not use if printed inner seal beneath cap is missing or broken.

Distributed by: GSK Consumer Healthcare,Warren, NJ 07059

Trademarks are owned by or licensed to the GSK group of companies.

©2022 GSK group of companies or its licensor.